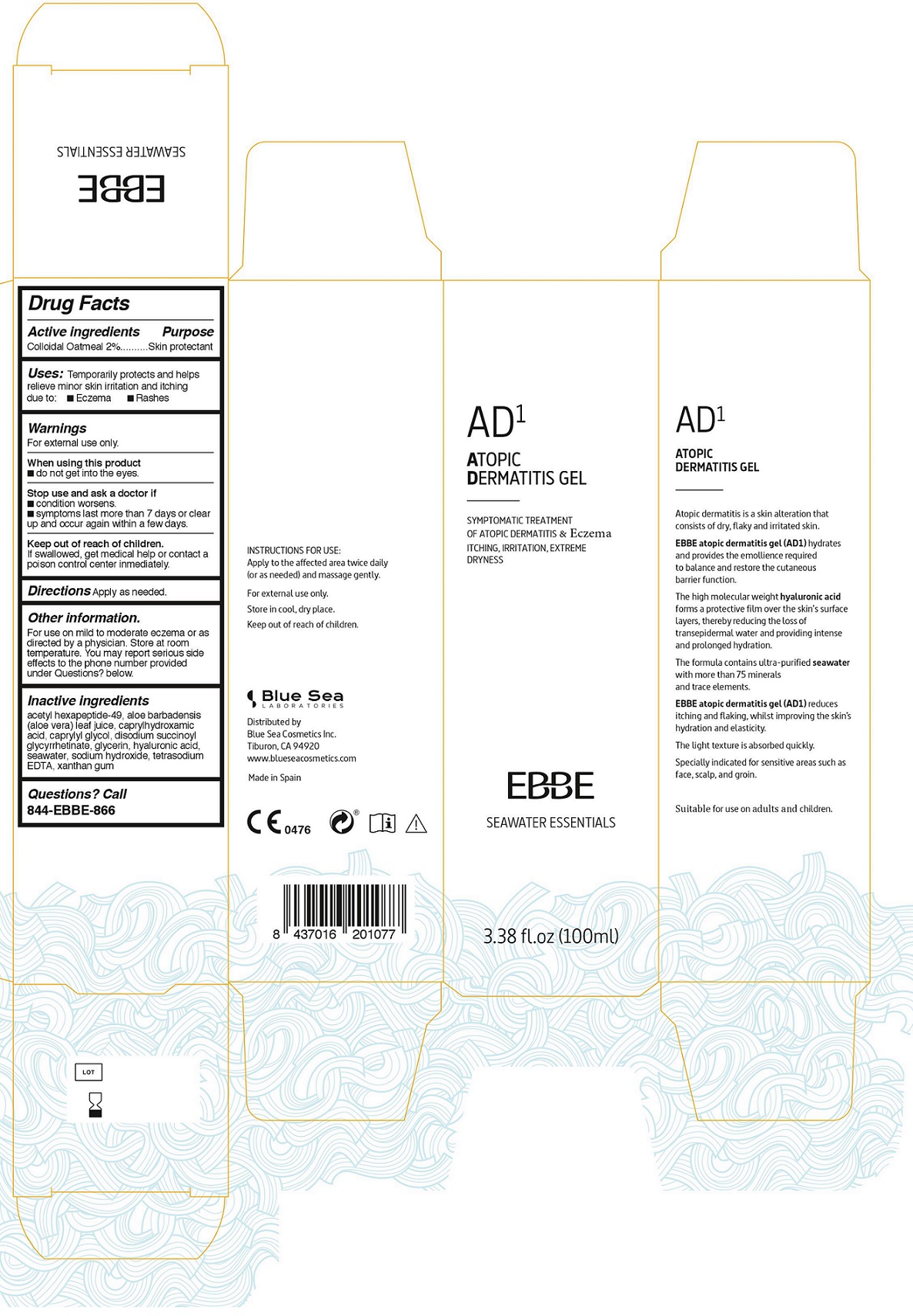 DRUG LABEL: EBBE
NDC: 71051-101 | Form: GEL
Manufacturer: BLUE SEA LABORATORIES SL.
Category: otc | Type: HUMAN OTC DRUG LABEL
Date: 20161105

ACTIVE INGREDIENTS: OATMEAL 2 g/100 mL
INACTIVE INGREDIENTS: ACETYL HEXAPEPTIDE-49; ALOE VERA LEAF; CAPRYLHYDROXAMIC ACID; CAPRYLYL GLYCOL; CARBENOXOLONE SODIUM; GLYCERIN; HYALURONIC ACID; SODIUM CHLORIDE; SODIUM HYDROXIDE; EDETATE SODIUM; XANTHAN GUM

AD1 ECZEMA GEL
EBBE SEAWATER ESSENTIALS

Active ingredients

Colloidal Oatmeal 2%

Purpose

Skin protectant

Uses

Temporarily protects and helps relieve minor skin irritation and itching due to: ■ Eczema ■ Rashes

Warnings

For external use only.

When using this product

■ do not get into the eyes.

Stop use and ask a doctor if

■ condition worsens.

■ symptoms last more than 7 days or clear up and occur again within a few days.

Keep out of reach of children.

If swallowed, get medical help or contact a poison control center immediately.

Directions

Apply as needed.

Inactive ingredients

acetyl hexapeptide-49, aloe barbadensis (aloe vera) leaf juice, caprylhydroxamic acid, caprylyl glycol, disodium succinoyl glycyrrhetinate, glycerin, hyaluronic acid, seawater, sodium hydroxide, tetrasodium EDTA, xanthan gum

Other information

For use on mild to moderate eczema or as directed by a physician. Store at room temperature. You may report serious side effects to the phone number provided under Questions? below.

Questions? Call

844-EBBE-866

INSTRUCTIONS FOR USE: Apply to the affected area twice daily (or as needed) and massage gently.

Store in cool, dry place

AD^1 ATOPIC DERMATITIS GEL

Atopic dermatitis is a skin alteration that consists of dry, flaky and irritated skin.

EBBE atopic dermatitis gel (AD1) hydrates and provides the emollience required to balance and restore the cutaneous barrier function.

The high molecular weight hyaluronic acid forms a protective film over the skin’s surface layers, thereby reducing the loss of transepidermal water and providing intense and prolonged hydration.

The formula contains ultra-purified seawater with more than 75 minerals and trace elements.

EBBE atopic dermatitis gel (AD1) reduces itching and flaking, whilst improving the skin’s hydration and elasticity.

The light texture is absorbed quickly.

Specially indicated for sensitive areas such as face, scalp, and groin.

Suitable for use on adults and children.

Distributed by

Blue Sea Cosmetics Inc.

Tiburon, CA 94920

www.blueseacosmetics.com

Made in Spain